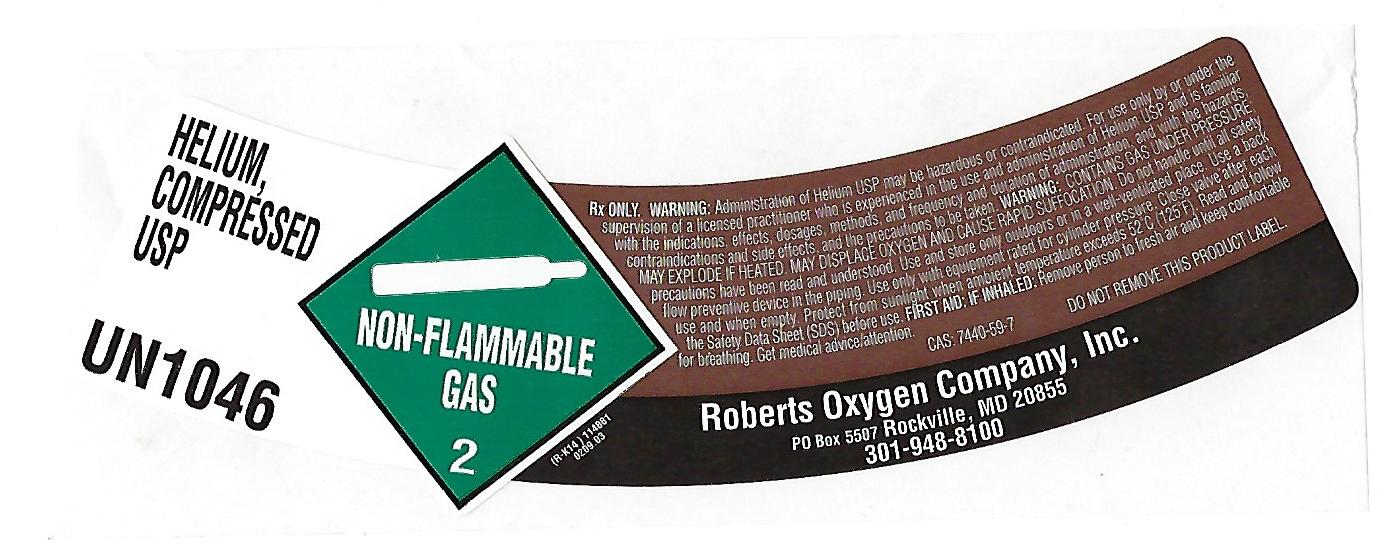 DRUG LABEL: Helium
NDC: 46123-800 | Form: GAS
Manufacturer: Roberts Oxygen Company, Inc.
Category: prescription | Type: HUMAN PRESCRIPTION DRUG LABEL
Date: 20251117

ACTIVE INGREDIENTS: HELIUM 990 mL/1 L

Helium-800

PACKAGE LABEL

HELIUM,
COMPRESSED
USP
UN1046
NON-FLAMMABLE GAS 2
Rx ONLY. WARNING:Administration of Helium USP may be hazardous or contraindicated. For use only by or under the supervision of a licensed practitioner who is experienced in the use and administration of Helium USP and is familiar with the indications, effects, dosages, methods, and frequency and duration of administration, and the hazards, contraindications and side effects and the precautions to be taken. WARNING:CONTAINS GAS UNDER PRESSURE; MAY EXPLODE IF HEATED. MAY DISPLACE OXYGEN AND CAUSE RAPID SUFFOCATION. Do not handle until all safety precautions have been read and understood. Use and store only outdoors or in a well-ventilated place. Use a back flow preventative device in the piping. Use only with equipment rated for cylinder pressure. Close valve after each use and when empty. Protect from sunlight when ambient temperature exceeds 52ºC (125ºF). Read and follow the Safety Data Sheet (SDS) before use. FIRST AID: IF INHALED:Remove person to fresh air and keep comfortable for breathing. Get medical advice/attention.
CAS: 7440-59-7 DO NOT REMOVE THIS PRODUCT LABEL.
Roberts Oxygen Company, Inc.
PO BOX 5507 Rockville, MD 20855
301-948-8100